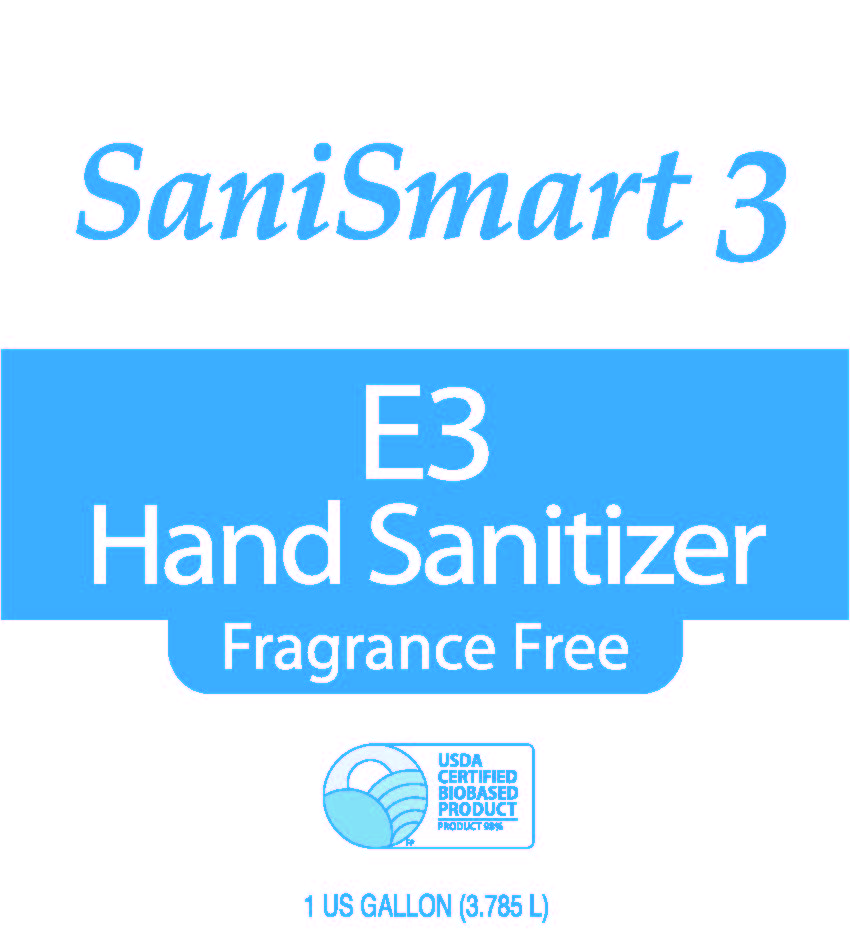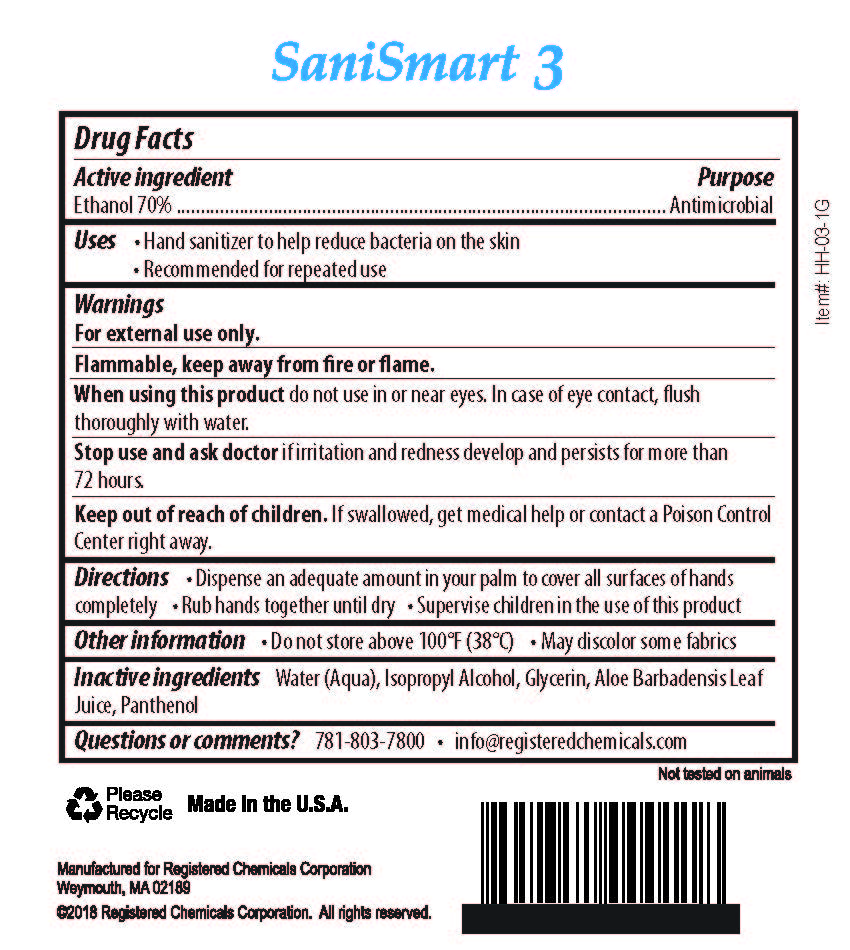 DRUG LABEL: SaniSmart 3
NDC: 72130-003 | Form: LIQUID
Manufacturer: Registered Chemicals Corporation
Category: otc | Type: HUMAN OTC DRUG LABEL
Date: 20180314

ACTIVE INGREDIENTS: ALCOHOL 70 g/100 mL
INACTIVE INGREDIENTS: WATER; ISOPROPYL ALCOHOL; GLYCERIN; ALOE VERA LEAF; PANTHENOL

Active ingredient

Ethanol 70%

Purpose

Antimicrobial

INDICATIONS AND USAGE

Uses •For hand washing to decrease bacteria on the skin

•Recommended for repeated use

Warnings

For external use only.

Flammable, keep away from fire or flame.

When using this product avoid contact with eyes. In case of eye contact, flush eyes

thoroughly with water.

Stop use and ask a doctor if irritation or redness develop, or if condition persists for more

than 72 hours.

Keep out of reach of children. If swallowed, get medical help or contact a

Poison Control Center right away.

DOSAGE AND ADMINISTRATION

Directions •Dispense an adeqaute amount in your palm to cover all surfaces of hands

completely. •Rub hands together until dry •Supervise children in the use of this product.

Other information •Do not store above 100° F (38° C) •May discolor some fabrics

INACTIVE INGREDIENT

Inactive ingredients Water (Aqua), Isopropyl Alcohol, Glycerin, Aloe Barbadensis Leaf

Juice Panthenol

Questions or comments? 781-03-7800 •info@registeredchemicals.com